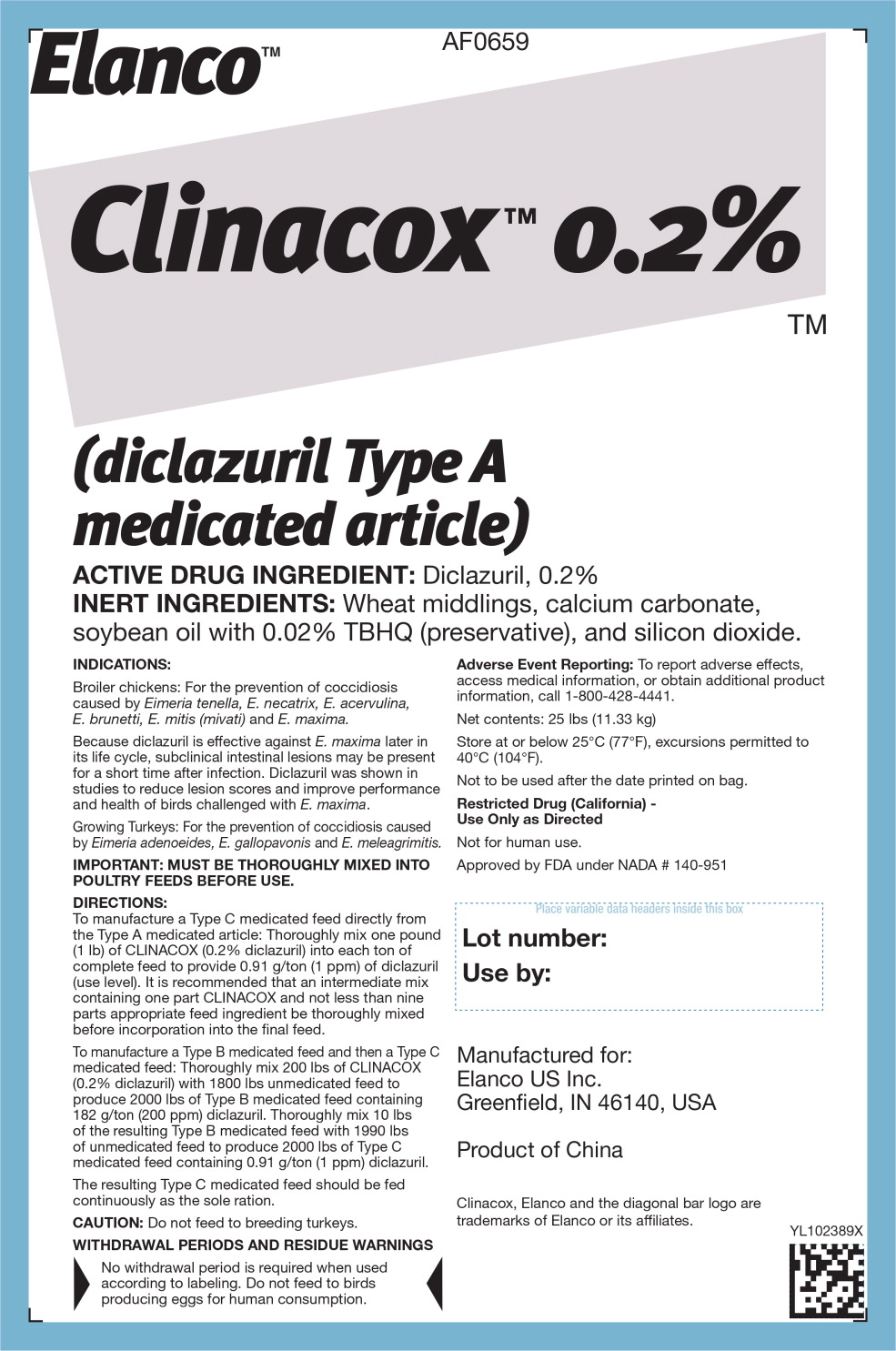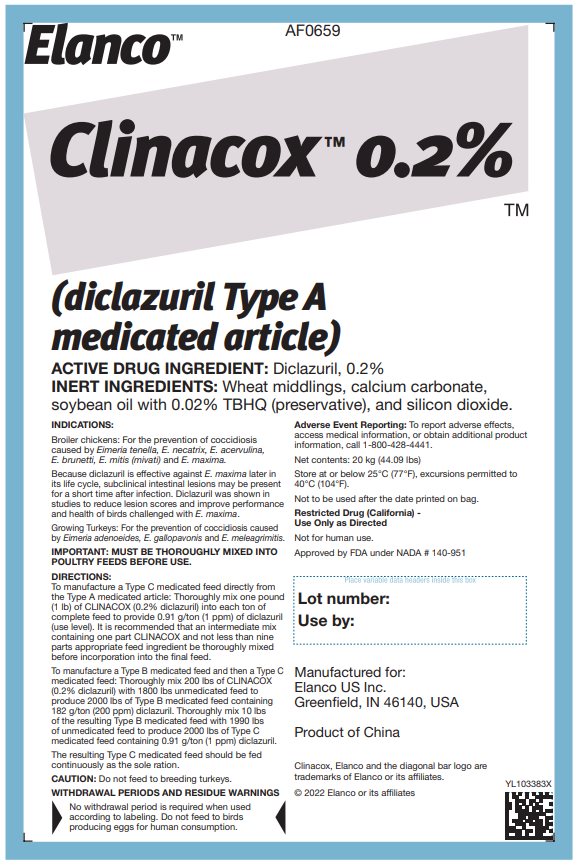 DRUG LABEL: Clinacox
NDC: 58198-0659 | Form: GRANULE
Manufacturer: Elanco US Inc.
Category: animal | Type: OTC TYPE A MEDICATED ARTICLE ANIMAL DRUG LABEL
Date: 20230424

ACTIVE INGREDIENTS: Diclazuril 0.9 g/1 kg

INDICATIONS:

Broiler chickens: For the prevention of coccidiosis caused by Eimeria tenella, E. necatrix, E. acervulina, E. brunetti, E. mitis (mivati) and E. maxima.

Because diclazuril is effective against E. maxima later in its life cycle, subclinical intestinal lesions may be present for a short time after infection. Diclazuril was shown in studies to reduce lesion scores and improve performance and health of birds challenged with E. maxima.

Growing Turkeys: For the prevention of coccidiosis caused by Eimeria adenoeides, E. gallopavonis and E. meleagrimitis.

IMPORTANT: MUST BE THOROUGHLY MIXED INTO POULTRY FEEDS BEFORE USE.

DIRECTIONS:

To manufacture a Type C medicated feed directly from the Type A medicated article: Thoroughly mix one pound (1 lb) of CLINACOX (0.2% diclazuril) into each ton of complete feed to provide 0.91 g/ton (1 ppm) of diclazuril (use level). It is recommended that an intermediate mix containing one part CLINACOX and not less than nine parts appropriate feed ingredient be thoroughly mixed before incorporation into the final feed.

To manufacture a Type B medicated feed and then a Type C medicated feed: Thoroughly mix 200 lbs of CLINACOX (0.2% diclazuril) with 1800 lbs unmedicated feed to produce 2000 lbs of Type B medicated feed containing 182 g/ton (200 ppm) diclazuril. Thoroughly mix 10 lbs of the resulting Type B medicated feed with 1990 lbs of unmedicated feed to produce 2000 lbs of Type C medicated feed containing 0.91 g/ton (1 ppm) diclazuril. The resulting Type C medicated feed should be fed continuously as the sole ration.

CAUTION: Do not feed to breeding turkeys.

WITHDRAWAL PERIODS AND RESIDUE WARNINGS

No withdrawal period is required when used according to labeling. Do not feed to birds producing eggs for human consumption.

Adverse Event Reporting: To report adverse effects, access medical information, or obtain additional product information, call 1-800-428-4441.

Net contents: 25 lbs (11.33 kg)
Net contents: 20 kg (44.09 lbs)

Store at or below 25°C (77°F), excursions permitted to 40°C (104°F).

Not to be used after the date printed on bag.

Restricted Drug (California) - Use Only as Directed

Not for human use.

Approved by FDA under NADA # 140-951

Manufactured for:
Elanco US Inc.
Greenfield, IN 46140, USA

Product of China

Clinacox, Elanco and the diagonal bar logo are trademarks of Elanco or its affiliates.

© 2022 Elanco or its affiliates

YL102389X
YL103383X

Principal Display Panel - 25 lbs Bag Label

AF0659

Elanco™

Clinacox 0.2%

(diclazuril Type A
medicated article)

ACTIVE DRUG INGREDIENT: Diclazuril, 0.2%

INERT INGREDIENTS: Wheat middlings, calcium carbonate, soybean oil with 0.02% TBHQ (preservative), and silicon dioxide.

Principal Display Panel - 20 kg Bag Label

AF0659

Elanco™

Clinacox 0.2%

(diclazuril Type A
medicated article)

ACTIVE DRUG INGREDIENT: Diclazuril, 0.2%

INERT INGREDIENTS: Wheat middlings, calcium carbonate, soybean oil with 0.02% TBHQ (preservative), and silicon dioxide.